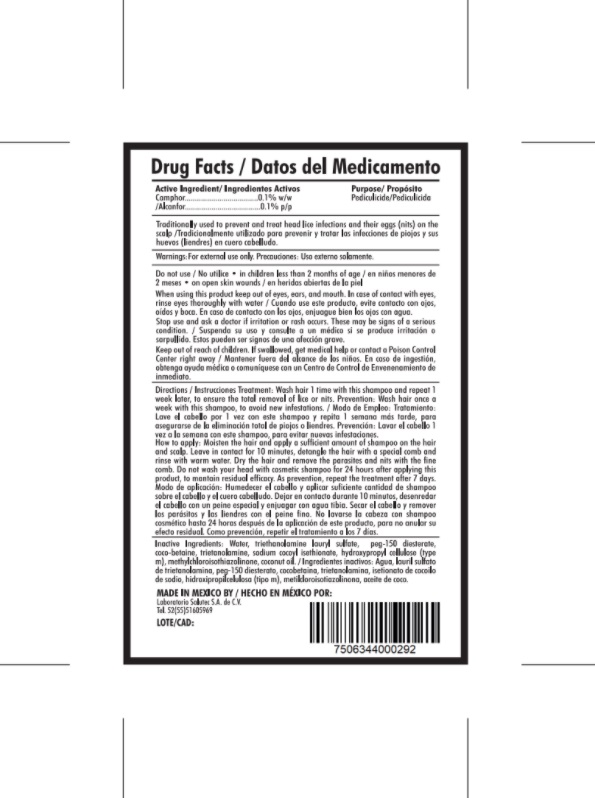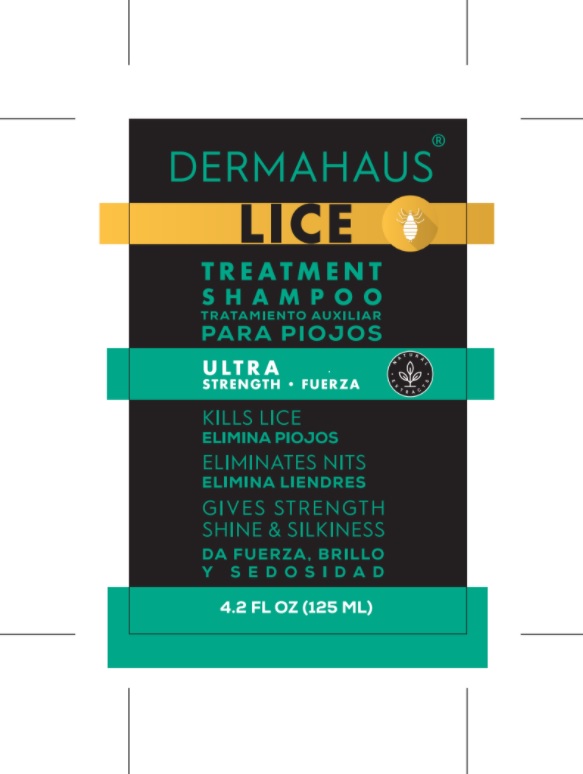 DRUG LABEL: Dermahaus
NDC: 79289-005 | Form: SHAMPOO
Manufacturer: Laboratorio Salutec, S.A. de C.V.
Category: otc | Type: HUMAN OTC DRUG LABEL
Date: 20200918

ACTIVE INGREDIENTS: CAMPHOR (SYNTHETIC) 0.001 g/100 mL
INACTIVE INGREDIENTS: COCONUT OIL 0.0002 g/100 mL; METHYLCHLOROISOTHIAZOLINONE 0.1 g/100 mL; TRIETHANOLAMINE LAURYL SULFATE 37.09 g/100 mL; PEG-150 DISTEARATE 4.5 g/100 mL; SODIUM COCOYL ISETHIONATE 1 g/100 mL; WATER 51.8 mL/100 mL; TROLAMINE 2 g/100 mL; COCO-BETAINE 3 g/100 mL; HYDROXYPROPYL CELLULOSE (TYPE M) 0.5 g/100 mL

ACTIVE INGREDIENT

Coconut Oil

Camphor

Purpose: Pediculicide, Lice treatment

INDICATIONS AND USAGE

Lice treatment shampoo kills lice and eliminates nits. Used to prevent and treat head lice infections and their eggs.

WARNINGS

For external use only.Keep out of reach of children.

When using this product keep out of eyes, ears and mouth. In case of contact with eyes rinse thoroughly with water.
If swallowed, get medical help or contact poison control center right away.

Stop use and ask a doctor if irritation or rash occurs.

DO NOT USE

On open skin wounds.
In children less than 2 months of age.

Do not wash your head with cosmetic shampoo for 24 hours after applying this product, to mantein residual efficacy.

Keep out of reach of children. If swallowed, get medical help or contact poison control center right away.

DOSAGE AND ADMINISTRATION

Treatment- Moisten hair 1 time with this shampoo and repeat 1 week later, to ensure the total removal of lice or nits.
Prevention - Wash hair once a week with this shampoo, avoid new infestations.
How to apply - Moisten the hair and apply a sufficient amount of shampoo on the hair and scalp. Leave in contact for 10 minutes, detangle the hair with a special comb and rinse with warm water. Dry the hair and remove the parasites and nits with the fine comb. Do not wash your head with cosmetic shampoo for 24 hours after applying this product, to mantein residual efficacy. As prevention, repeat the treatment after 7 days.

STORAGE AND HANDLING

Store between 15-30C (59-86F)
Avoid freezing and excessive heat above 40C (104F)

INACTIVE INGREDIENT

PEG-150 Distearate
Sodium Cocoyl Isethionate
Triethanoolamine Lauryl Sulfate
Tromlamine
Coco-Betaine
Hydroxypropyl Cellulose (TypeM)
Methylchloroisothiazolinone
Water

PACKAGE LABEL

125 mL NDC: 79289-005-01